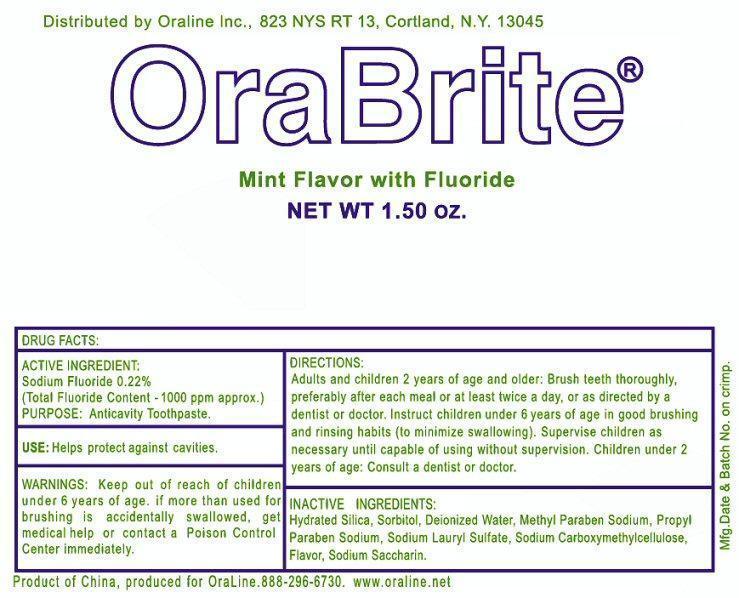 DRUG LABEL: OraBrite
NDC: 54371-471 | Form: PASTE, DENTIFRICE
Manufacturer: Oraline, Inc.
Category: otc | Type: HUMAN OTC DRUG LABEL
Date: 20121114

ACTIVE INGREDIENTS: SODIUM FLUORIDE 0.22 g/100 g
INACTIVE INGREDIENTS: HYDRATED SILICA; SORBITOL; WATER; METHYLPARABEN SODIUM; PROPYLPARABEN SODIUM; SODIUM LAURYL SULFATE; CARBOXYMETHYLCELLULOSE SODIUM; SACCHARIN SODIUM

Active Ingredient

DRUG FACTS

ACTIVE INGREDIENT:

Sodium Fluoride 0.22%

(Total Fluoride Content - 1000 ppm approx.)

Purpose

PURPOSE: Anticavity Toothpaste.

Keep Out Of Reach Of Children

WARNINGS: Keep out of reach of children under 6 years of age. If more than used for brushing is accidentally swallowed, get medical help or contact a Poison Control Center immediately.

Use

USE: Helps protect against cavities.

Warnings

WARNINGS: Keep out of reach of children under 6 years of age. If more than used for brushing is accidentally swallowed, get medical help or contact a Poison Control Center immediately.

Directions

Adults and children 2 tears of age and older: Brush teeth thoroughly, preferably after each meal or at least twice a day, or as directed by a dentist or doctor. Instruct children under 6 years of age in god brushing and rinsing habits. (to minimize swallowing). Supervise children as necessary until capable of using without supervision. Children under 2 years of age: Consult a dentist or doctor.

Inactive Ingredients

Hydrated Silica, Sorbitol, Deionized Water, Methyl Paraben Sodium, Propyl Paraben Sodium, Sodium Lauryl Sulfate, Sodium Carboxymethylcellulose, Flavor, Sodium Saccharin.

Package Label

Distributed by Oraline Inc., 823 NYS RT 13, Cortland, N.Y. 13045

OraBrite

Mint Flavor with Fluoride

NET WT 1.50 oz.

Mfg. Date and Batch No. on crimp.

Product of China, produced for Oraline. 888-296-6730. www.oraline.net